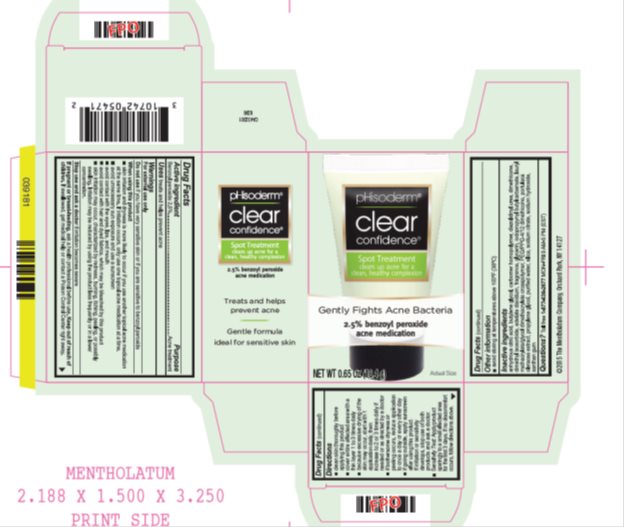 DRUG LABEL: Phisoderm Clear Confidence Spot Treatment
NDC: 10742-8293 | Form: CREAM
Manufacturer: The Mentholatum Company
Category: otc | Type: HUMAN OTC DRUG LABEL
Date: 20241217

ACTIVE INGREDIENTS: BENZOYL PEROXIDE 25 mg/1 g
INACTIVE INGREDIENTS: ANHYDROUS CITRIC ACID; BUTYLENE GLYCOL; CARBOMER HOMOPOLYMER TYPE C (ALLYL PENTAERYTHRITOL CROSSLINKED); DIAZOLIDINYL UREA; DIMETHICONE; DIMETHYL ISOSORBIDE; EDETATE DISODIUM; GLYCERIN; IODOPROPYNYL BUTYLCARBAMATE; LAURYL METHACRYLATE/GLYCOL DIMETHACRYLATE CROSSPOLYMER; PEG/PPG-4/12 DIMETHICONE; PURSLANE; PROPYLENE GLYCOL; WATER; SILICON DIOXIDE; SODIUM CITRATE; SODIUM HYDROXIDE; XANTHAN GUM

Drug Facts - Phisoderm Clear Confidence Spot Treatment

Active ingredient

Benzoyl peroxide 2.5%

Purpose

Acne treatment

Uses

treats and helps prevent acne

Warnings

For external use only

Do Not Use if you

- have very sensitive skin
- are sensitive to benzoyl peroxide

When using this product

- skin irritation and dryness is more likely to occur if you use another topical acne medication at the same time. If irritation occurs, only use one topical acne medication at a time.
- avoid unnecessary sun exposure and use a sunscreen
- avoid contact with the eyes, lips, and mouth
- avoid contact with hair and dyed fabrics, which may be bleached by this product
- skin irritation may occur, characterized by redness, burning, itching, peeling, or possibly swelling. Irritation may be reduced by using this product less frequently or in a lower concentration.

Stop use and ask a doctor if

irritation becomes severe

If pregnant or breast-feeding

ask a health professional before use.

Keep out of reach of children

If swallowed, get medical help or contact a Poison Control Center right away.

Directions

- clean skin thoroughly before applying this product
- cover entire affected area with a thin layer 1 to 3 times daily
- because excessive drying of the skin may occur, start with 1 application daily, then gradually increase to 2 or 3 times daily if needed or as directed by a doctor
- if bothersome dryness or peeling occurs, reduce application to once a day or every other day
- if going outside, apply sunscreen after using this product. If irritation or sensitivity develops, stop use of both products and ask a doctor.
- Sensitivity Test: Apply product sparingly to a small affected area for the first 3 days. If no discomfort occurs, follow directions above.

Other information

avoid storing at temperatures above 100°F (38°C)

Inactive Ingredients

anhydrous citric acid, butylene glycol, carbomer homopolymer, diazolidinyl urea, dimethicone, dimethyl isosorbide, edetate disodium, fragrance, glycerin, iodopropynyl butylcarbamate, lauryl methacrylate/glycol dimethacrylate crosspolymer, PEG/PPG-4/12 dimethicone, portulaca oleracea extract, propylene glycol, purified water, silica, sodium citrate, sodium hydroxide, xanthan gum

Questions?

Toll free 1-877-636-2677 MON-FRI 9 AM-5 PM (EST)